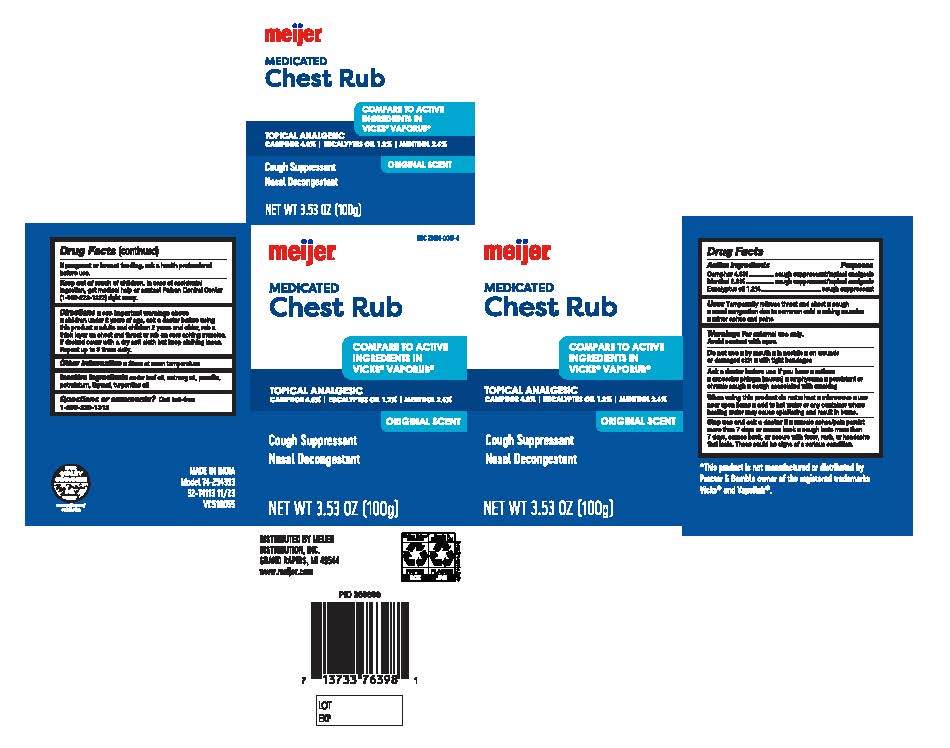 DRUG LABEL: Meijer Medicated Chest Rub
NDC: 79481-0047 | Form: GEL
Manufacturer: Meijer Distribution
Category: otc | Type: HUMAN OTC DRUG LABEL
Date: 20240522

ACTIVE INGREDIENTS: CAMPHOR (SYNTHETIC) 4.8 g/100 g; MENTHOL 2.6 g/100 g; EUCALYPTUS OIL 1.2 g/100 g
INACTIVE INGREDIENTS: PARAFFIN; THYMOL; TURPENTINE OIL; CEDAR LEAF OIL; NUTMEG OIL; PETROLATUM

Meijer Medicated Chest Rub

Active Ingredient

Camphor 4.8%

Menthol 2.6%

Eucalyptus oil 1.2%

Purposes

cough suppressant / topical analgesic

Uses

Uses Temporarily relieves throat and chest ■cough ■ nasal congestion due to common cold ■aching muscles ■ minor aches and pains

Warning

For external use only

Avoid contact with eyes

Do not use ■by mouth ■ in nostrils ■on wounds
or damaged skin ■ with tight bandages

Ask a doctor before use if you have ■asthma ■excessive phlegm (mucus) ■emphysema ■persistent or chronic cough ■cough associated with smoking

When using this product do not ■heat ■microwave ■use near open flame ■ Add hot water or any container where heating water may cause splattering and result in burns.

Stop use and ask a doctor if ■muscle aches/pain persists more than 7 days()(comes back ■cough lasts more than 7 days, comes back, or occurs with fever, rash, or headache that lasts. These could be signs of a serious condition.

If pregnant or breastfeeding

ask a health professional before use

Keep out of reach of children. In case of accidental ingestion, get medical help, or contact Poison Control Center (1-800-222-1222) right away

Directions

Directions ■ see important warnings above
■children under 2 years of age, ask a doctor before using this product ■adults and children 2 years and older, rub a thick layer on chest and throat or rub on sore aching muscles. If desired cover it with a dry soft cloth but keep clothing loose. Repeat up to 3 times daily.

Other Information

Store at room temperature

Inactive Ingredients

cedar leaf oil, nutmeg oil, paraffin, petrolatum, thymol, turpentine oil

Questions or comments?

Call toll free 1-866-326-1313